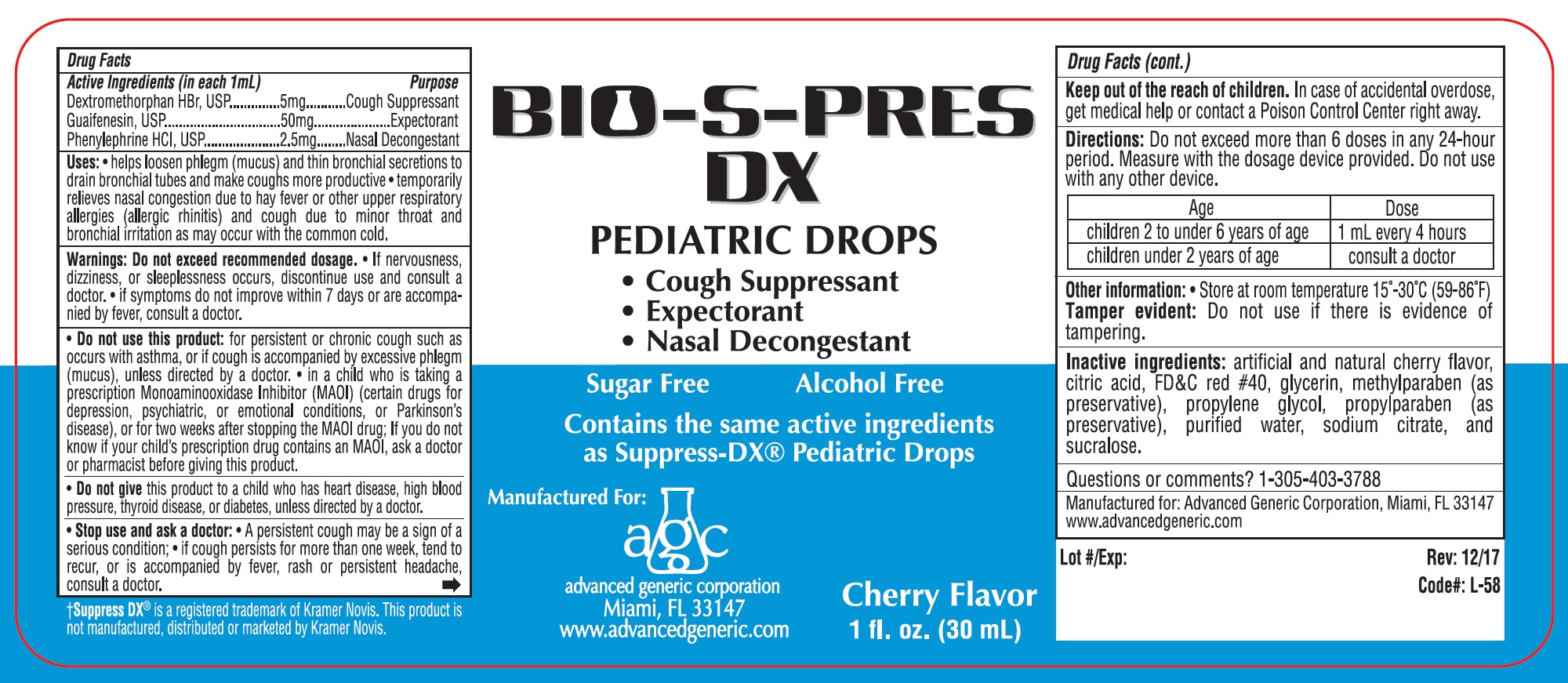 DRUG LABEL: Bio-S-Pres
NDC: 45737-230 | Form: SOLUTION/ DROPS
Manufacturer: Advanced Generic Corporation
Category: otc | Type: HUMAN OTC DRUG LABEL
Date: 20241220

ACTIVE INGREDIENTS: DEXTROMETHORPHAN HYDROBROMIDE 5 mg/1 mL; GUAIFENESIN 50 mg/1 mL; PHENYLEPHRINE HYDROCHLORIDE 2.5 mg/1 mL
INACTIVE INGREDIENTS: CITRIC ACID MONOHYDRATE; ANHYDROUS CITRIC ACID; FD&C RED NO. 40; GLYCERIN; METHYLPARABEN; PROPYLENE GLYCOL; PROPYLPARABEN; WATER; SODIUM CITRATE; SUCRALOSE

AGC-BioSPressDX 230

Active Ingredients (in each 1mL) Purpose

Dextromethorphan HBr, 5 mg ................................. Cough Suppressant

Guaifenesin, 50 mg ................................................ Expectorant

Phenylephrine HCl, 2.5 mg ...................................... Nasal Decongestant

Purpose

Cough Suppressant

Expectorant

Nasal Decongestant

Warnings:

Do not exceed recommended dosage.

- If nervousness, dizziness, or sleeplessness occurs, discontinue use and consult a doctor.
- If symptoms do not improve within 7 days or accompanied by fever, consult a doctor.

- Do not use this product:for persistent or chronic cough such as occurs with asthma, or if cough is accompanied by excessive phlegm (mucus), unless directed by a doctor.
- in a child who is taking a prescription Monoaminooxidase Inhibitor (MAOI) (certain drugs for depression, psychiatric or emotional conditions, or Parkinson's disease), or for two weeks after stopping the MAOI drug; If you do not know if your child's prescription drug contains an MAOI, ask a doctor or pharmacist before giving this product.
- Do not givethis product to child who has heart disease, high blood pressure, thyroid disease, or diabetes, unless directed by a doctor.
- Stop use and ask a doctor:
- A persistent cough may be a sign of a serious condition;
- If cough persists for more than one week, tend to recur, or is accompanied by fever, rash or persistent headache, consult a doctor.

KEEP OUT OF REACH OF CHILDREN

Keep out of the reach of children.In case of accidental overdose, get medical help or contact a Poison Control Center right away.

DOSAGE AND ADMINISTRATION

Directions:Do not exceed more than 6 doses in any 24-hour period. Measure with the dosage device provided. Do not use with any other device.

Age | Dose
Children 2 to under 6 years of age | 1 mL every 4 hours
Children under 2 years of age | Consult a doctor

INACTIVE INGREDIENT

Inactive ingredients:Artificial and natural Cherry Flavor, Citric Acid, FD and C Red No. 40, Glycerin, Methyl Paraben (as preservative), Propylene Glycol, Propylparaben (as preservative), Purified Water, sodium citrate, and sucralose

Questions or comments?1-305-403-3788

Uses

helps loosen phlegm (mucus) and thin bronchial secretions to drain bronchial tubes and make coughs more productive
temporarily relieves nasal congestion due to hay fever or other upper respiratory allergies (allergic rhinitis) and cough due to minor throat and bronchial irritation as may occur with the common cold.